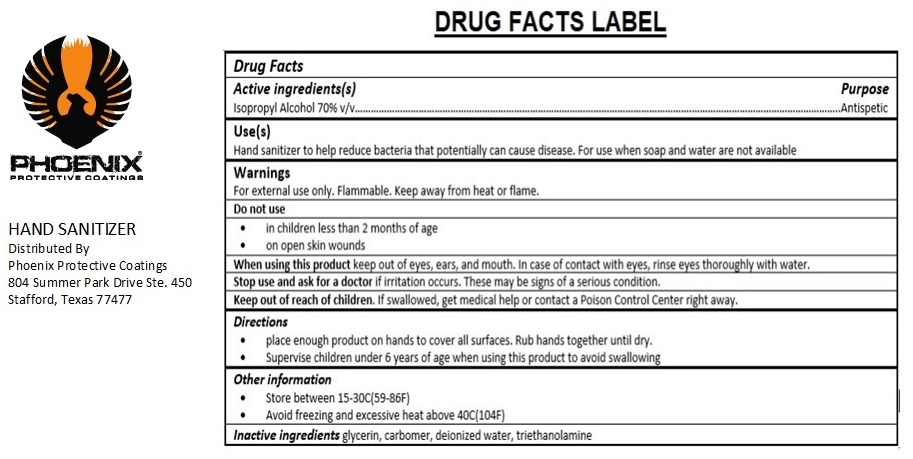 DRUG LABEL: Phoenix Hand Sanitizer
NDC: 75547-905 | Form: LIQUID
Manufacturer: Phoenix Mcbs Llc
Category: otc | Type: HUMAN OTC DRUG LABEL
Date: 20200422

ACTIVE INGREDIENTS: ISOPROPYL ALCOHOL 70 mL/100 mL
INACTIVE INGREDIENTS: GLYCERIN; CARBOMER HOMOPOLYMER, UNSPECIFIED TYPE; WATER; TROLAMINE

Phoenix Hand Sanitizer

Active ingredient(s)

Isopropyl Alcohol 70% v/v

Purpose

Antiseptic

Use(s)

Hand sanitizer to help reduce bacteria that potentially can cause disease. For use when soap and water are not available

Warnings

For external use only. Flammable. Keep away from heat or flame.

Do not use
• in children less than 2 months of age
• on open skin wounds

When using this product keep out of eyes, ears, and mouth. In case of contact with eyes, rinse eyes thoroughly with water.

Stop use and ask for a doctor if irritation occurs. These may be signs of a serious condition.

Keep out of reach of children. If swallowed, get medical help or contact a Poison Control Center right away.

Directions

• place enough product on hands to cover all surfaces. Rub hands together until dry.
• Supervise children under 6 years of age when using this product to avoid swallowing

Other information

• Store between 15-30C(59-86F)
• Avoid freezing and excessive heat above 40C(104F)

INACTIVE INGREDIENT

Inactive ingredients glycerin, carbomer, deionized water, triethanolamine

Distributed By
Phoenix Protective Coatings
804 Summer Park Drive Ste. 450
Stafford, Texas 77477